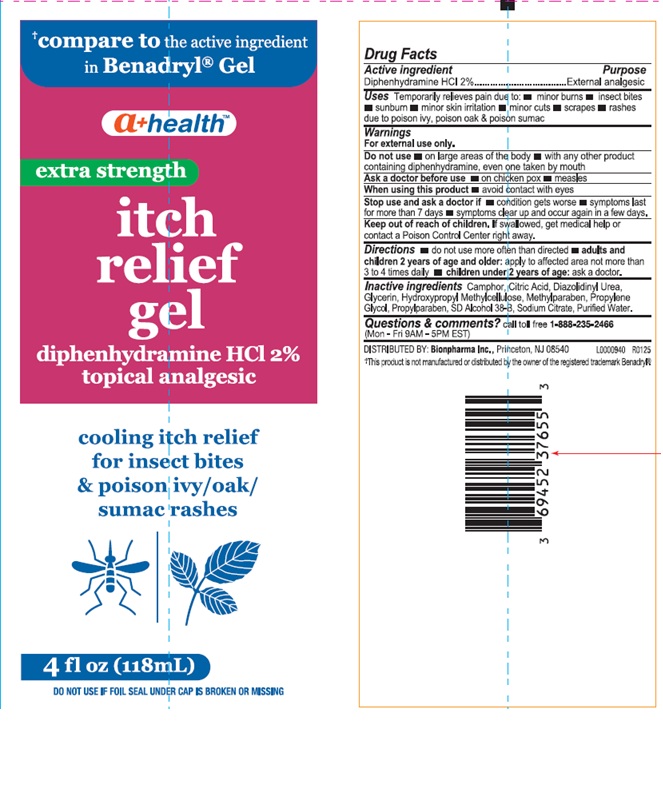 DRUG LABEL: A Health Itch Relief Gel
NDC: 69452-496 | Form: GEL
Manufacturer: Bionpharma, Inc.
Category: otc | Type: HUMAN OTC DRUG LABEL
Date: 20250620

ACTIVE INGREDIENTS: DIPHENHYDRAMINE HYDROCHLORIDE 2 mg/100 mL
INACTIVE INGREDIENTS: METHYLPARABEN; PROPYLPARABEN; PROPYLENE GLYCOL; ALCOHOL; DIAZOLIDINYL UREA; SODIUM CITRATE; WATER; GLYCERIN; ANHYDROUS CITRIC ACID; CAMPHOR (SYNTHETIC); HYPROMELLOSE, UNSPECIFIED

A+ Health Itch Relief Gel

Active Ingredient

Diphenhydramine HCl 2%

Purpose

External analgesic

Uses

Temporarily relieves pain due to: • minor burns • insect bites

• sunburn • minor skin irritation • minor cuts • scrapes • rashes

due to poison ivy, poison oak & poison sumac

Warnings

For external use only.

Do not use

• on large areas of the body • with any other product containing diphenhydramine, even one taken by mouth

Ask a doctor before use

• on chicken pox • measles

When using this product

• avoid contact with eyes

Stop use and ask a doctor if

• condition gets worse • symptoms last for more than 7 days • symptoms clear up and occur again in a few days.

Keep out of reach of children

If swallowed, get medical help or contact a Poison Control Center right away.

Directions

• do not use more often than directed • adults and
children 2 years of age and older: apply to affected area not more than
3 to 4 times daily • children under 2 years of age: ask a doctor.

Inactive ingredients

Camphor, Citric Acid, Diazolidnyl Urea,

Glycerin, Hydroxypropyl Methylcellulose, Methylparaben, Propylene

Glycol, Propylparaben, SD Alcohol 38-B, Sodium Citrate, Purified Water.

Questions and comments?

call toll free 1-888-235-2466 (Mon - Fri 9AM - 5PM EST)

DISTRIBUTED BY: Bionpharma Inc., Princeton, NJ 08540

L0000940 R0125

†This product is not manufactured or distributed by the owner of the registered trademark Benadryl†®

4 fl oz (118 mL) tube

† Compare to the active ingredient

in Benadryl® Gel

a+ healthTM

extra strength

itch

relief

gel

diphenhydramine HCl 2%

topical analgesic

cooling itch relief

for insect bites

& poison ivy/oak/

sumac rashes

4 fl oz (118 mL)

DO NOT USE IF FOIL UNDER CAP IS BROKEN OR MISSING